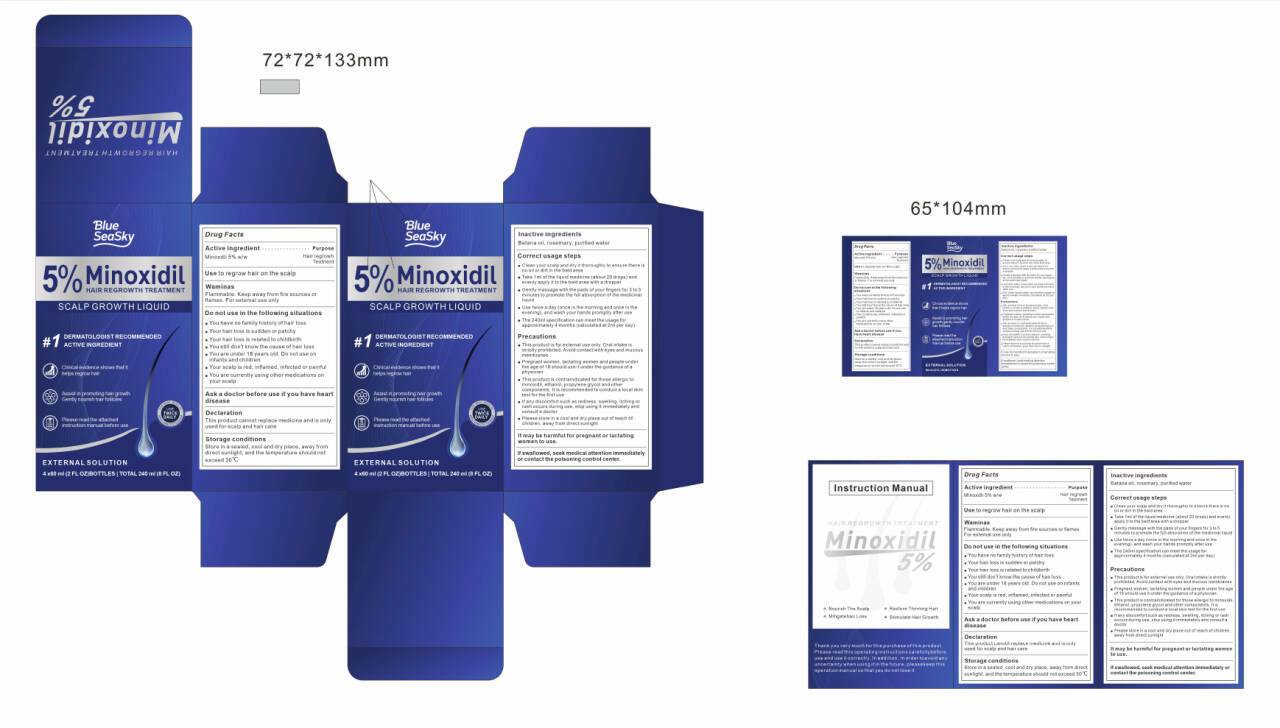 DRUG LABEL: 5% Minoxidil Hair Care Solution
NDC: 87376-001 | Form: LIQUID
Manufacturer: Shenzhen Linglong Trading Co., Ltd.
Category: otc | Type: HUMAN OTC DRUG LABEL
Date: 20260123

ACTIVE INGREDIENTS: MINOXIDIL 5 g/100 mL
INACTIVE INGREDIENTS: ROSMARINUS OFFICINALIS (ROSEMARY) LEAF OIL; WATER

87376-001

Active Ingredient(s)

Minoxdli 5% w/w

Purpose

Hair regrowh Teotnent

Use

Use to regrow hair on the scalp

Warnings

Flammable. Keep away from fire sources or flames. For extemal use only

Do not use

You have no family history of hair loss
Your hair loss is sudden or patchy
Your hair loss is related to childbirth
You still don't know the cause of hair loss
You are under 18 years old. Do not use on infants and children
Your scalp is red, inflamed, infected or painful
You are currently using other medications on your scalp

WHEN USING

In case of contact with eyes, rinse eyes thoroughly with water.

STOP USE

1. This product is contraindicated for those allergic to minoxidil, ethanol, propylene glycol and other
components. It is recommended to conduct a local skin test for the first use
2. If any discomfort such as redness, swelling, itching or rash occurs during use, stop using it immediately and
consult a doctor

Keep out of reach of children. If swallowed, get medical help or contact a Poison Control Center right away.

Directions

This product cannot replace medicine and is only used for scalp and hair care

Other information

Store in a sealed, cool and dry place, away from
direct sunlight, and the temperature should not
exceed 30℃

Inactive ingredients

Batana oil, rosemary, purified water